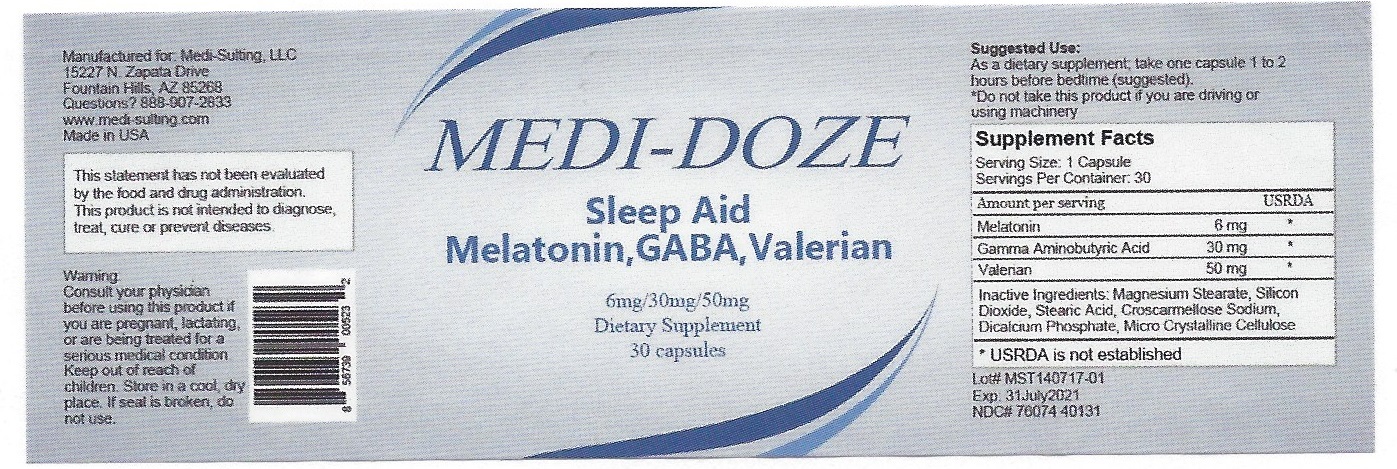 DRUG LABEL: MEDI-DOZE
NDC: 76074-401 | Form: TABLET
Manufacturer: Two Hip Consulting, LLC
Category: other | Type: DIETARY SUPPLEMENT
Date: 20170808

ACTIVE INGREDIENTS: MELATONIN 6 mg/1 1; .GAMMA.-AMINOBUTYRIC ACID 30 mg/1 1; VALERIAN 50 mg/1 1
INACTIVE INGREDIENTS: MAGNESIUM STEARATE; SILICON DIOXIDE; STEARIC ACID; CROSCARMELLOSE SODIUM; CALCIUM PHOSPHATE, DIBASIC, ANHYDROUS; CELLULOSE, MICROCRYSTALLINE

HEALTH CLAIM

SLEEP AID

PRECAUTIONS

*DO NOT TAKE THIS PRODUCT IF YOU ARE DRIVING OR USING MACHINERY

WARNING:

CONSULT YOUR PHYSICIAN BEFORE USING THIS PRODUCT IF YOU ARE PREGNANT, LACTATING, OR ARE BEING TREATED FOR A SERIOUS MEDICAL CONDITION. KEEP OUT OF REACH OF CHILDREN.

SAFE HANDLING WARNING

STORE IN A COOL, DRY PLACE. IF SEAL IS BROKEN, DO NOT USE.

STATEMENT OF IDENTITY

MEDI-DOZE

SLEEP AID

MELATONIN, GABA, VALERIAN

DOSAGE AND ADMINISTRATION

AMOUNT PER SERVING

MELATONIN 6 MG

GAMMA AMINOBUTYRIC ACID 30 MG

VALERIAN 50 MG

ONE TABLET 1 TO 2 HOURS BEFORE BEDTIME (SUGGESTED).